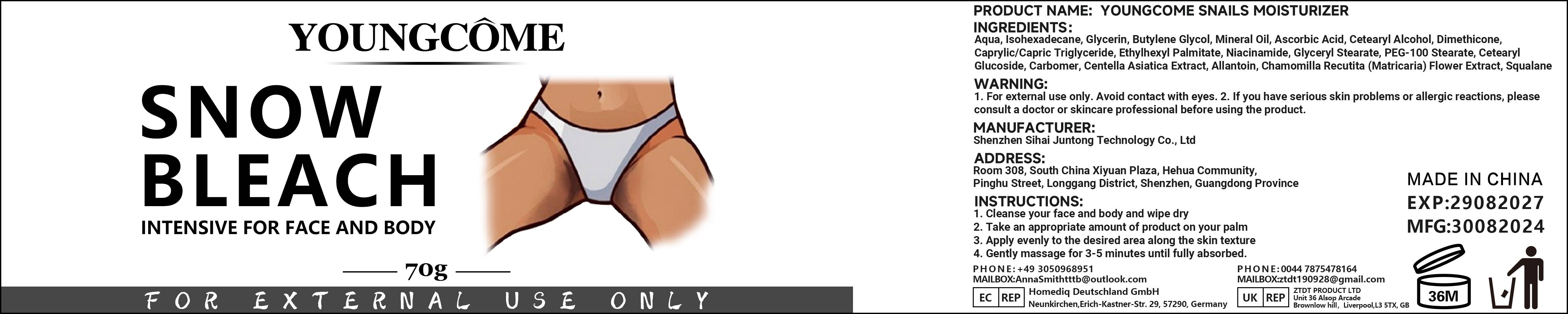 DRUG LABEL: YOUNGCOME SNOW BLEACH
NDC: 84350-008 | Form: CREAM
Manufacturer: Shenzhen Sihai Juntong Technology Co., Ltd
Category: otc | Type: HUMAN OTC DRUG LABEL
Date: 20240920

ACTIVE INGREDIENTS: SQUALANE 1 g/100 mg
INACTIVE INGREDIENTS: WATER

ACTIVE INGREDIENT

Ascorbic Acid 5%

INACTIVE INGREDIENT

Water 5%

PURPOSE

Whitening and moisturizing

WARNINGS

WARNING.1. For external use only Avoid contact with eyes. 2. lf you have serious skin problems or allergic reactions, pleaseconsult a
doctor or skincare professional before using the product.

lf you have allergic reactions, stop to use

WHEN USING

1. Cleanse your face and body and wipe dry2. Take an appropriate amount of product on your palm3. Apply evenly to the desired area along the skin texture4. Gently massage for 3-5 minutes until fully absorbed.

Keep out of reach of children

INDICATIONS AND USAGE

1. Cleanse your face and body and wipe dry2. Take an appropriate amount of product on your palm3. Apply evenly to the desired area along the skin texture4.Gently massage for 3-5 minutes until fully absorbed.

DOSAGE AND ADMINISTRATION

appropriate amount

PACKAGE LABEL

70g NDC:84350-008-01